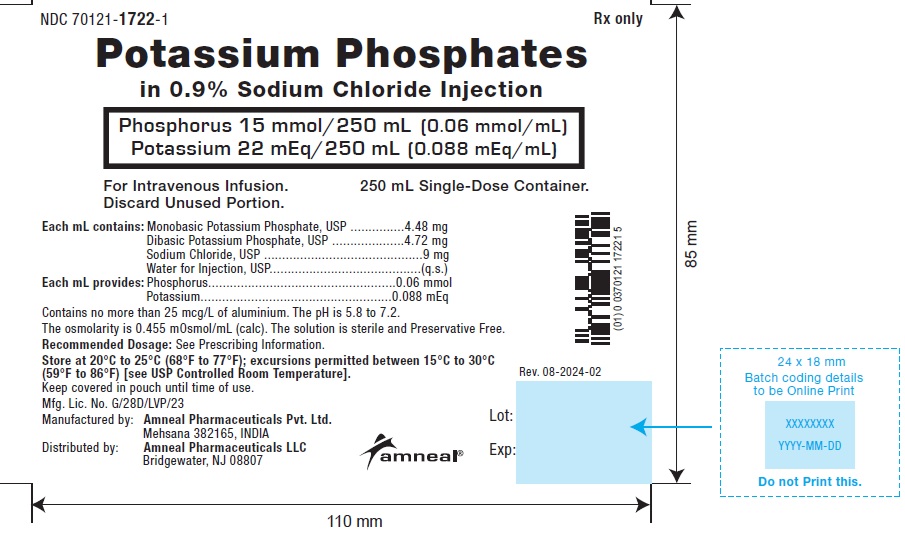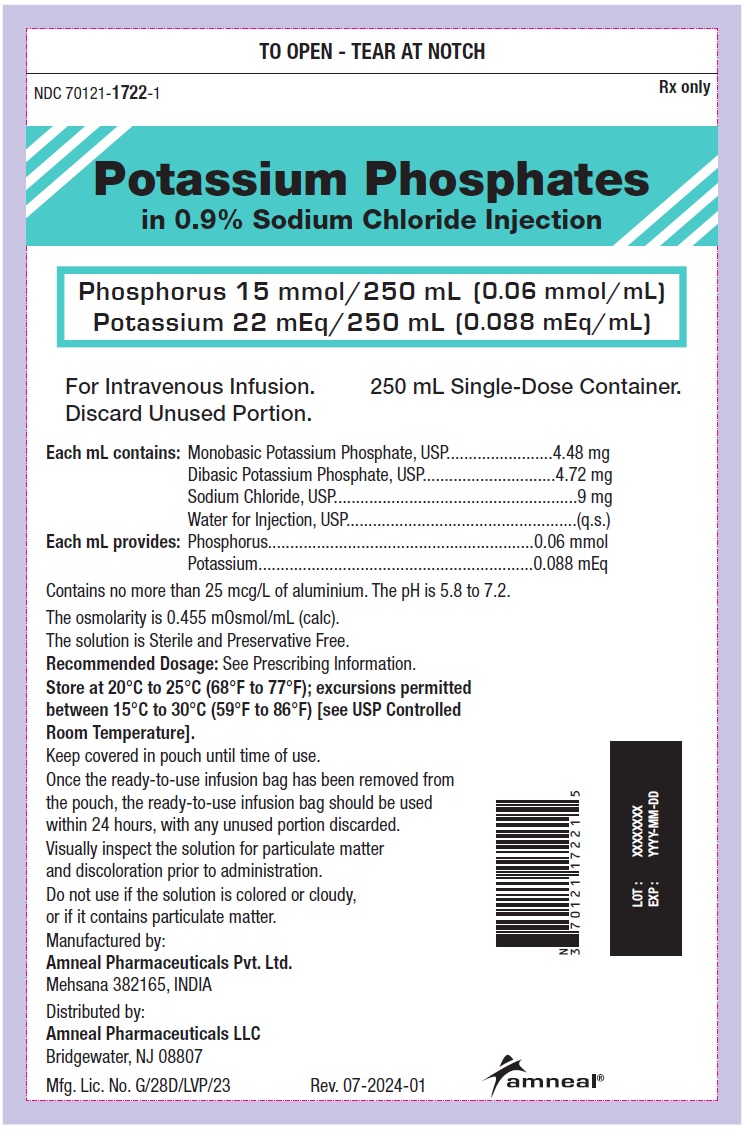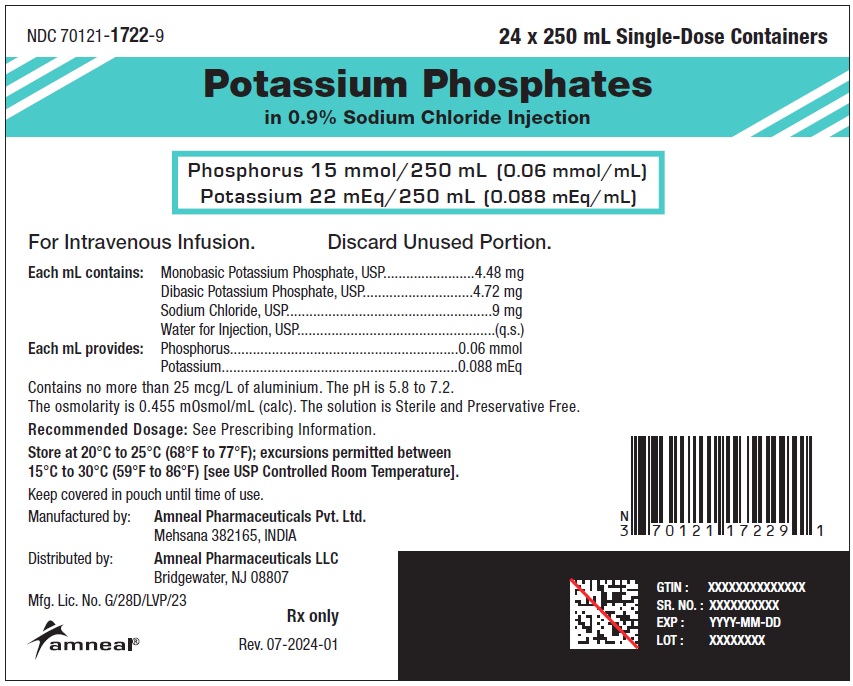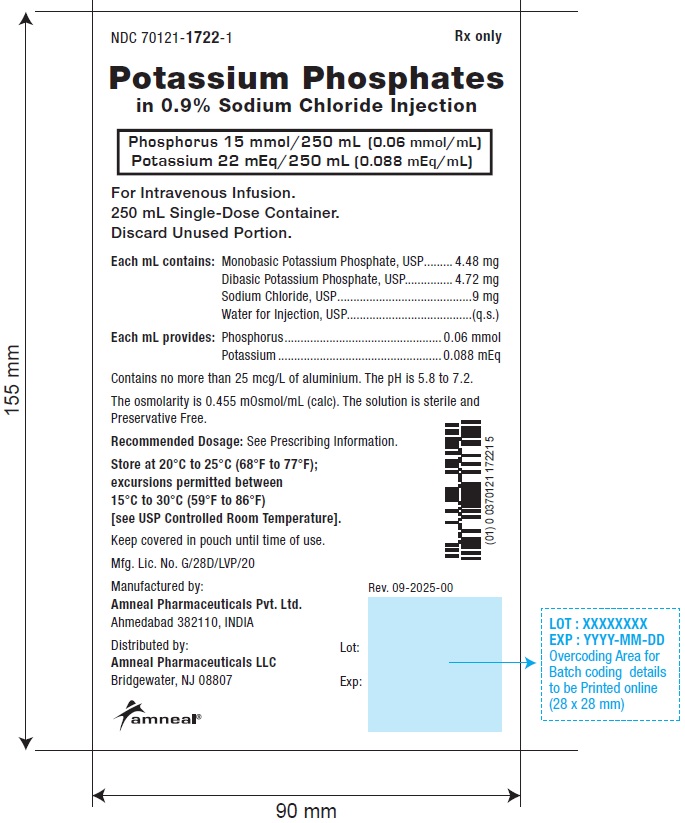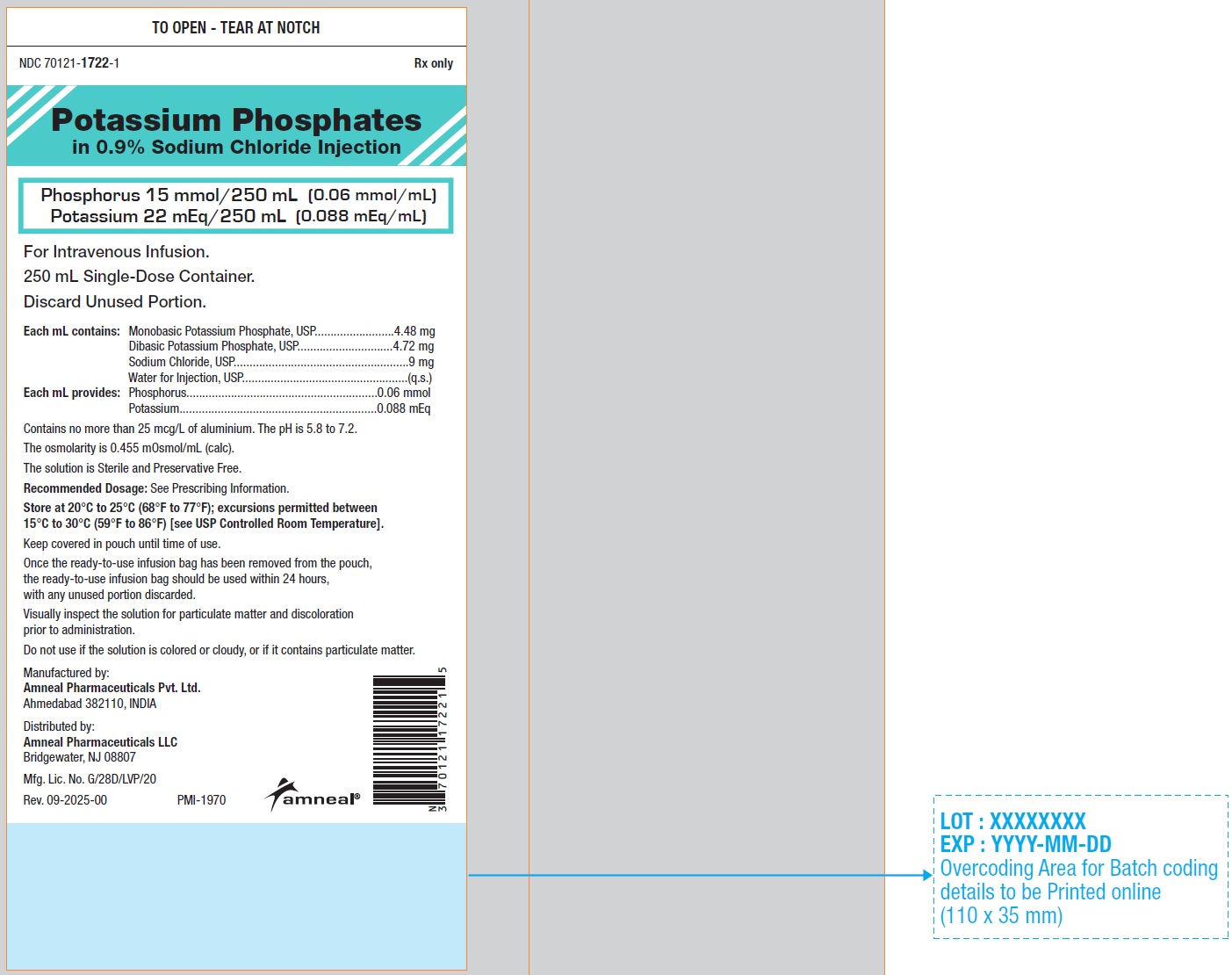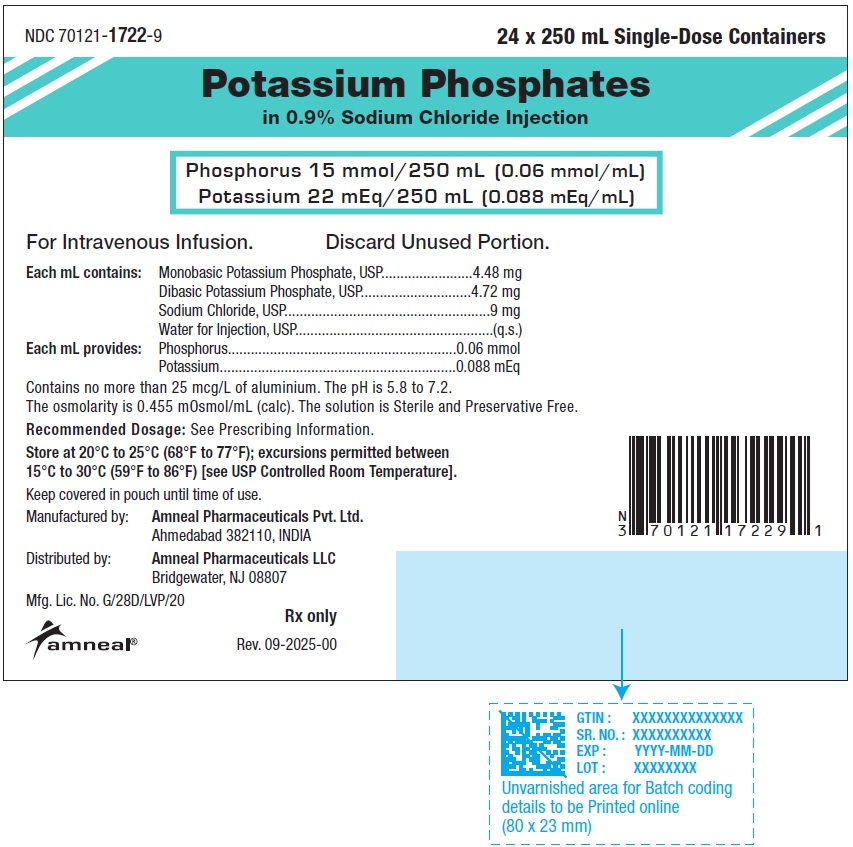 DRUG LABEL: POTASSIUM PHOSPHATES
NDC: 70121-1722 | Form: INJECTION
Manufacturer: Amneal Pharmaceuticals LLC
Category: prescription | Type: HUMAN PRESCRIPTION DRUG LABEL
Date: 20250901

ACTIVE INGREDIENTS: POTASSIUM PHOSPHATE, MONOBASIC 4.48 mg/1 mL; POTASSIUM PHOSPHATE, DIBASIC 4.72 mg/1 mL
INACTIVE INGREDIENTS: SODIUM CHLORIDE 9 mg/1 mL; WATER

HIGHLIGHTS OF PRESCRIBING INFORMATION

These highlights do not include all the information needed to use POTASSIUM PHOSPHATES IN SODIUM CHLORIDE INJECTION safely and effectively. See full prescribing information for POTASSIUM PHOSPHATES IN SODIUM CHLORIDE INJECTION.
POTASSIUM PHOSPHATES IN SODIUM CHLORIDE injection, for intravenous use
Initial U.S. Approval: 1983

1 INDICATIONS AND USAGE

Potassium Phosphates in Sodium Chloride Injection is a phosphorus replacement product indicated as a source of phosphorus to correct hypophosphatemia in adults and pediatric patients who weigh 40 kg or greater when oral or enteral replacement is not possible, insufficient or contraindicated. (1)

2 DOSAGE AND ADMINISTRATION

Important Preparation Instructions

- Do NOT dilute prior to administration. (2.1)
- Use this potassium phosphates in sodium chloride injection product only in patients who require the entire 15 mmoL phosphorus dose (potassium 22 mEq) and not any fraction thereof. Otherwise, consider an alternative formulation of potassium phosphate. (2.1)
  Important Administration Instructions
- Potassium Phosphates in Sodium Chloride Injection is only for administration to a patient with a serum potassium concentration less than 4 mEq/dL; otherwise, use an alternative source of phosphorus. (2.2)
- Use of this potassium phosphates in sodium chloride injection product increases the risk of hyperkalemia in patients weighing less than 40 kg, including life threatening cardiac events. (5.3)
- See full prescribing information for important administration instructions. (2.2)

Recommended Dosage

- This product contains phosphorus 15 mmol and potassium 22 mEq (phosphorus 0.06 mmol/mL and potassium 0.088 mEq/mL). (2.3)
- Monitor serum phosphorus, potassium, calcium and magnesium concentrations. (2.3)
- See full prescribing information for recommendations on initial or single dosing, repeated dosing, concentration and infusion rate. (2.1, 2.2, 2.3)

3 DOSAGE FORMS AND STRENGTHS

Injection:

- Phosphorus 15 mmol/250 mL (0.06 mmol/mL) and Potassium 22 mEq/250 mL (0.088 mEq/mL) clear, colorless solution filled in a single-dose intravenous infusion bag. (3)

4 CONTRAINDICATIONS

- hyperkalemia. (4)
- hyperphosphatemia. (4)
- hypercalcemia or significant hypocalcemia. (4)
- severe renal impairment (eGFR less than 30 mL/min/1.73 m^2) or end stage renal disease. (4)

5 WARNINGS AND PRECAUTIONS

- Serious Cardiac Adverse Reactions with Rapid Intravenous Administration: Do NOT dilute prior to administration; do not exceed the recommended infusion rate. Continuous electrocardiographic (ECG) monitoring may be needed during infusion. (2.2, 5.1)
- Pulmonary Embolism due to Pulmonary Vascular Precipitates: If signs of pulmonary distress occur, stop the infusion and initiate a medical evaluation. (5.2)
- Hyperkalemia: Increased risk in patients with renal impairment, severe adrenal insufficiency, or treated with drugs that increase potassium. Patients with cardiac disease may be more susceptible. Do not exceed the maximum daily amount of potassium or the recommended infusion rate. Continuous ECG monitoring may be needed during infusion. (5.3, 7.1)
- Hyperphosphatemia and Hypocalcemia: Monitor serum phosphorus and calcium concentrations during and following infusion. (5.4)
- Hypomagnesemia: Reported in patients with hypercalcemia and diabetic ketoacidosis. Monitor serum magnesium concentrations during treatment. (5.5)
- Vein Damage and Thrombosis: Infuse concentrated or hypertonic solutions through a central catheter. (2.1, 2.3, 5.6)

6 ADVERSE REACTIONS

Adverse reactions include hyperkalemia, hyperphosphatemia, hypocalcemia, and hypomagnesemia. (6)

To report SUSPECTED ADVERSE REACTIONS, contact Amneal Pharmaceuticals LLC at 1-877-835-5472 or FDA at 1-800-FDA-1088 or www.fda.gov/medwatch.

7 DRUG INTERACTIONS

Use of Other Medications that Increase Potassium: Avoid use in patients receiving such products. If use cannot be avoided, closely monitor serum potassium concentrations. (5.3, 7.1)

FULL PRESCRIBING INFORMATION

1 INDICATIONS AND USAGE

Potassium Phosphates in Sodium Chloride Injection is indicated as a source of phosphorus to correct hypophosphatemia in adults and pediatric patients who weigh 40 kg or greater when oral or enteral replacement is not possible, insufficient, or contraindicated.

2 DOSAGE AND ADMINISTRATION

2.1 Important Preparation Instructions

- Potassium Phosphates in Sodium Chloride Injection is for intravenous infusion into a central or peripheral vein. No dilution of this product is required.
- Use this potassium phosphates in sodium chloride injection product only in patients who require the entire 15 mmoL phosphorus dose (potassium 22 mEq) and not any fraction thereof.
- If a dose of potassium phosphate is required that does not equal 15 mmoL of Potassium phosphates in Sodium Chloride Injection, then an alternative formulation of potassium phosphates should be considered.

- Visually inspect the solution for particulate matter and discoloration prior to administration. Do not administer unless solution is clear.
- Always inspect the solution container before and after removal from the pouch.
- Place the solution container on a clean, flat surface. Remove the solution container from the pouch.
- Check the solution container for leaks by squeezing firmly. Discard if leaks are found.
- Immediately before inserting the infusion set, remove twist-off port from the infusion bag.
- Use a non-vented infusion set or close the air-inlet on a vented set.
- Close the roller clamp of the infusion set.
- Hold the base of the infusion port, twist, and push spike until fully inserted. The infusion port contains a membrane that helps prevent leakage after removing the spike. The infusion port is not intended to be spiked more than once.
- Suspend solution container from hanger hole.
- For single-dose only. Discard unused portion.

2.2 Important Administration Instructions

- Check serum potassium and calcium concentrations prior to administration. Normalize the serum calcium level before administering Potassium Phosphates in Sodium Chloride Injection [see Contraindications (4), Warnings and Precautions (5.3, 5.4)].
- Potassium Phosphates in Sodium Chloride Injection is only for administration to a patient with a serum potassium concentration less than 4 mEq/dL [see Warnings and Precautions (5.3)]. If the potassium concentration is 4 mEq/dL or more, use an alternative source of phosphorus.
- Use of this potassium phosphates in sodium chloride injection product increases the risk of hyperkalemia in adults and pediatric patients weighing less than 40 kg, including life threatening cardiac events [see Warnings and Precautions (5.3)].
- Do not infuse with calcium-containing intravenous fluids [see Warnings and Precautions (5.4)].
- The rate of administration may be dependent on the patient and the specific institution policy [see Dosage and Administration (2.2)].
- When administered peripherally, a generally recommended maximum concentration is phosphorus 6.8 mmol/100 mL (potassium 10 mEq/100 mL).

2.3 Recommended Dosage

- This potassium phosphates in sodium chloride injection product contains phosphorus 15 mmol and potassium 22 mEq (phosphorus 0.06 mmol/mL and potassium 0.088 mEq/mL). Patients with body weight greater than 96 kg will receive a dose of less than 0.16 mmol/kg phosphorus.
- The phosphorus doses in Table 1 are general recommendations for an initial or single dose of potassium phosphates and are intended for most patients [see Warnings and Precautions (5.1)].
- Consider overall volume status of the patient when determining whether Potassium Phosphates in Sodium chloride Injection is an appropriate product for phosphorus replacement.

- In patients with moderate renal impairment (eGFR ≥ 30 mL/min/1.73 m^2 to < 60 mL/min/1.73 m^2), start at the low end of the dose range [see Use in Specific Populations (8.6)].
- Monitor serum phosphorus, potassium, calcium, and magnesium concentrations.

TABLE 1: Recommended Initial or Single Doses of Potassium Phosphates to Correct Hypophosphatemia in Adults and Pediatric Patients Weighing 40 kg or Greater

Serum Phosphorus Concentrationa | Phosphorus Dosageb, c | Corresponding Potassium Content
1.8 mg/dL to lower end of the reference rangea | 0.16 mmol/kg to 0.31 mmol/kg | Potassium 0.23 mEq/kg to 0.46 mEq/kg
1 mg/dL to 1.7 mg/dL | 0.32 mmol/kg to 0.43 mmol/kg | Potassium 0.47 mEq/kg to 0.63 mEq/kg
Less than 1 mg/dL | 0.44 mmol/kg to 0.64 mmol/kgc | Potassium 0.64 mEq/kg to 0.94 mEq/kg
a Serum phosphorus reported using 2.5 mg/dL as the lower end of the reference range for healthy adults and pediatric patients 12 months of age and older. Serum phosphorus concentrations may vary depending on the assay used and the laboratory reference range.
b Weight is in terms of actual body weight. Limited information is available regarding dosing of patients significantly above ideal body weight; consider using an adjusted body weight for these patients.
c This single-dose preparation of Potassium Phosphates in Sodium Chloride Injection contains phosphorus 15 mmol and potassium 22 mEq. Additional dose(s) following the initial dose may be needed in some patients.

Intravenous Infusion Rate

- The infusion rate is dependent upon whether administration will be through a peripheral or central venous catheter. The maximum recommended infusion rates are shown in Table 2 for adults and pediatric patients 12 years of age and older.

TABLE 2: Maximum Recommended Infusion Rate of Potassium Phosphates in Sodium Chloride Injection for Adults and Pediatric Patients Weighing 40 kg or Greater

Route of Administration | Maximum Infusion Rate
Peripheral Venous Catheter | phosphorus 6.8 mmol/hour; (potassium 10 mEq/hour)
Central Venous Catheter | phosphorus 15 mmol/hour; (potassium 22 mEq/hour)

Continuous electrocardiographic (ECG) monitoring and infusion through a central venous catheter is recommended for infusion rates higher than potassium 10 mEq/hour.

Repeated Dosing

Additional dose(s) following the initial dose may be needed in some patients. Prior to administration of additional doses, assess the patient clinically, obtain serum phosphorus, calcium, and potassium concentrations and adjust the dose accordingly.

3 DOSAGE FORMS AND STRENGTHS

Potassium Phosphates in 0.9% Sodium Chloride Injection is a clear, colorless solution filled in a single-dose intravenous infusion bag and supplied as:

- Phosphorus 15 mmol/250 mL (0.06 mmol/mL) and Potassium 22 mEq/250 mL (0.088 mEq/mL)

4 CONTRAINDICATIONS

Potassium Phosphates in Sodium Chloride Injection is contraindicated in patients with:

- hyperkalemia [see Warnings and Precautions (5.3)]
- hyperphosphatemia [see Warnings and Precautions (5.4)]
- hypercalcemia or significant hypocalcemia [see Warnings and Precautions (5.4)]
- severe renal impairment (eGFR less than 30 mL/min/1.73m^2) or end stage renal disease [see Warnings and Precautions (5.3)]

5 WARNINGS AND PRECAUTIONS

5.1 Serious Cardiac Adverse Reactions with Rapid Intravenous Administration

Intravenous administration of potassium phosphates to correct hypophosphatemia in single-doses of phosphorus 50 mmol and greater and/or at rapid infusion rates (over 1 to 3 hours) has resulted in death, cardiac arrest, cardiac arrhythmia (including QT prolongation), hyperkalemia, hyperphosphatemia and seizures [see Overdosage (10)].

Potassium Phosphates in Sodium Chloride Injection is for intravenous infusion. No dilution of this product is required. The maximum initial or single-dose of potassium phosphates to correct hypophosphatemia is phosphorus 45 mmol (potassium 66 mEq). The recommended infusion rate for administration through a peripheral venous catheter is approximately phosphorus 6.8 mmol/hour (potassium 10 mEq/hour). Continuous electrocardiographic (ECG) monitoring is recommended for higher infusion rates [see Dosage and Administration (2.1, 2.2)].

5.2 Pulmonary Embolism Due to Pulmonary Vascular Precipitates

Pulmonary vascular emboli and pulmonary distress related to precipitates in the pulmonary vasculature have been described in patients receiving admixed products containing calcium and phosphate. The cause of precipitate formation has not been determined in all cases; however, in some fatal cases, pulmonary emboli occurred as a result of calcium phosphate precipitates. Precipitation has occurred following passage through an in-line filter; in vivo precipitate formation may also have occurred. If signs of pulmonary distress occur, stop the infusion and initiate a medical evaluation. In addition to inspection of the solution [see Dosage and Administration (2.3)], the infusion set and catheter should also periodically be checked for precipitates.

5.3 Hyperkalemia

Potassium Phosphates in Sodium Chloride Injection may increase the risk of hyperkalemia, including life-threatening cardiac events, especially when administered in excessive doses or by rapid intravenous infusion [see Warnings and Precautions (5.1)]. Patients with severe renal impairment and end stage renal disease are at increased risk of developing life-threatening hyperkalemia, when administered intravenous potassium [see Contraindications (4)]. Other patients at increased risk of hyperkalemia include those with severe adrenal insufficiency or treated concurrently with other drugs that cause or increase the risk of hyperkalemia [see Drug Interactions (7.1)]. Patients with cardiac disease may be more susceptible to the effects of hyperkalemia.

Consider the amount of potassium from all sources when determining the dose of Potassium Phosphates in Sodium Chloride Injection and do not exceed the maximum age-appropriate recommended daily amount of potassium. In patients with moderate renal impairment (eGFR ≥ 30 mL/min/1.73 m^2 to < 60 mL/min/1.73 m^2), start at the low end of the dose range and monitor serum potassium, phosphorus, calcium, and magnesium concentrations [see Dosage and Administration (2.2), Use in Specific Populations (8.6)].

When administering Potassium Phosphates in Sodium Chloride Injection to correct hypophosphatemia, check the serum potassium concentration prior to administration. If the potassium concentration is 4 mEq/dL or more, do not administer Potassium Phosphates in Sodium Chloride Injection and use an alternative source of phosphorus [see Dosage and Administration (2.1)].

The maximum initial or single-dose of potassium phosphates to correct hypophosphatemia is phosphorus 45 mmol (potassium 66 mEq). The recommended infusion rate of potassium through a peripheral venous catheter is 10 mEq/hour. Continuous electrocardiographic (ECG) monitoring is recommended for higher infusion rates of potassium [see Dosage and Administration (2.2)].

5.4 Hyperphosphatemia and Hypocalcemia

Hyperphosphatemia can occur with intravenous administration of potassium phosphates, especially in patients with renal impairment. Hyperphosphatemia can cause the formation of insoluble calcium phosphorus products with consequent hypocalcemia, neurological irritability with tetany, nephrocalcinosis with acute kidney injury and more rarely, cardiac irritability with arrhythmias.

Obtain serum calcium concentrations prior to administration and normalize the calcium before administering Potassium Phosphates in Sodium Chloride Injection. Potassium Phosphates in Sodium Chloride Injection is contraindicated in patients with hyperphosphatemia and/or hypercalcemia [see Contraindications (4)].

Monitor serum phosphorus and calcium concentrations during treatment with Potassium Phosphates in Sodium Chloride Injection [see Dosage and Administration (2.2)].

5.5 Hypomagnesemia

Intravenous infusion of phosphate has been reported to cause a decrease in serum magnesium (and calcium) concentrations when administered to patients with hypercalcemia and diabetic ketoacidosis. Monitor serum magnesium concentrations during treatment.

5.6 Vein Damage and Thrombosis

The infusion of potassium phosphates solutions into a peripheral vein may result in vein irritation, vein damage, and/or thrombosis. The primary complication of peripheral administration is venous thrombophlebitis, which manifests as pain, erythema, tenderness, or a palpable cord.

5.7 Laboratory Monitoring

Monitor serum phosphorus, potassium, calcium, and magnesium concentrations during treatment [see Dosage and Administration (2.2)].

6 ADVERSE REACTIONS

The following clinically significant adverse reactions are described elsewhere in the labeling:

- Hypomagnesemia [see Warnings and Precautions (5.5)]
- Vein Damage and Thrombosis [see Warnings and Precautions (5.6)]

The following adverse reactions in Table 3 have been reported in clinical studies or post-marketing reports in patients receiving intravenously administered potassium phosphates. Because some of these reactions were reported voluntarily from a population of uncertain size, it is not always possible to reliably estimate their frequency or establish a causal relationship to drug exposure.

TABLE 3: Adverse Reactions Reported in Clinical Studies or Post-marketing Reports with Intravenous Potassium Phosphates

System Organ Class | Adverse Reactions
Metabolism and Nutrition Disorders | pulmonary embolism due to pulmonary vascular precipitates [see Warnings and Precautions (5.2)], hyperkalemia [see Warnings and Precautions (5.3)], hyperphosphatemia [see Warnings and Precautions (5.4)], hypocalcemia [see Warnings and Precautions (5.4)], hypovolemia and osmotic diuresis
Cardiac Disorders | hypotension, arrhythmia, heart block, cardiac arrest, bradycardia, chest pain, ECG changes [see Warnings and Precautions (5.1)] and edema
Respiratory, Thoracic, and Mediastinal Disorders | dyspnea [see Warnings and Precautions (5.2)]
Renal and Urinary Disorders | acute phosphate nephropathy (i.e., nephrocalcinosis with acute kidney injury), decreased urine output and transition to chronic kidney disease [see Warnings and Precautions (5.4)]
Gastrointestinal Disorders | diarrhea, stomach pain
Musculoskeletal and Connective Tissue Disorders | weakness
Nervous System Disorders | confusion, lethargy, paralysis, paresthesia

7 DRUG INTERACTIONS

7.1 Other Products that Increase Serum Potassium

Administration of Potassium Phosphates in Sodium Chloride Injection to patients treated concurrently or recently with products that increase serum potassium (e.g., potassium-sparing diuretics, ACE inhibitors, angiotensin II receptor antagonists, digoxin, or the immunosuppressants tacrolimus and cyclosporine) increases the risk of severe and potentially fatal hyperkalemia, in particular in the presence of other risk factors for hyperkalemia [see Warnings and Precautions (5.3)]. Avoid use of Potassium Phosphates in Sodium Chloride Injection in patients receiving such products. If use cannot be avoided, closely monitor serum potassium concentrations [see Dosage and Administration (2.2)].

8 USE IN SPECIFIC POPULATIONS

8.1 Pregnancy

Risk Summary

Administration of the recommended dose of Potassium Phosphates in Sodium Chloride Injection is not expected to cause major birth defects, miscarriage, or adverse maternal or fetal outcomes. Consider potassium phosphate replacement if correction of hypophosphatemia via the enteral route is not possible (see Clinical Considerations). Animal reproduction studies have not been conducted with Potassium Phosphates in Sodium Chloride Injection.

The background risk of major birth defects and miscarriage for the indicated population is unknown. All pregnancies have a background risk of birth defect, loss, or other adverse outcomes. In the U.S. general population, the estimated background risk of major birth defects and miscarriage in clinically recognized pregnancies is 2% to 4% and 15% to 20%, respectively.

Clinical Considerations

Disease-associated Maternal and/or Embryo-Fetal Risk

Phosphorus is an essential mineral element. Intravenous replacement with potassium phosphate should be considered if a pregnant woman requires intravenous replacement to correct hypophosphatemia when the enteral route is not possible, insufficient or contraindicated.

8.2 Lactation

Risk Summary

Phosphorus and potassium are present in human milk. Administration of the recommended dose of Potassium Phosphates in Sodium Chloride Injection is not expected to cause harm to a breast-fed infant. There is no information on the effects of potassium phosphates on milk production. The development and health benefits of breastfeeding should be considered along with the mother’s clinical need for Potassium Phosphates in Sodium Chloride Injection and any potential adverse effects on the breastfed child from Potassium Phosphates in Sodium Chloride Injection or from underlying maternal condition.

8.4 Pediatric Use

Safety and effectiveness of Potassium Phosphates in Sodium Chloride Injection have been established in pediatric patients weighing 40 kg or more as a source of phosphorus to correct hypophosphatemia when oral or enteral replacement is not possible, insufficient, or contraindicated. However, this potassium phosphates in sodium chloride injection product is not approved for use in pediatric patients who weigh less than 40 kg because of the lack of an appropriate formulation.

8.5 Geriatric Use

In general, dose selection of Potassium Phosphates in Sodium Chloride Injection for an elderly patient should be cautious, starting at the low end of the dosing range because of the greater frequency of decreased hepatic, renal, or cardiac function and of concomitant disease or other drug therapy. It may be useful to monitor renal function during treatment [see Use in Specific Populations (8.6)].

8.6 Renal Impairment

Potassium and phosphorus are known to be substantially excreted by the kidney and the risk of adverse reactions to Potassium Phosphates in Sodium Chloride Injection may be greater in patients with impaired renal function [see Warnings and Precautions (5.3, 5.4)].

Potassium Phosphates in Sodium Chloride Injection is contraindicated due to the risk of hyperkalemia in patients with severe renal impairment (eGFR less than 30 mL/min/1.73 m^2) or end stage renal disease [see Contraindications (4)].

In patients with moderate renal impairment (eGFR ≥ 30 mL/min/1.73 m^2 to < 60 mL/min/1.73 m^2), start at the low end of the dosage range and monitor serum potassium, phosphorus, calcium, and magnesium concentrations [see Dosage and Administration (2.2)].

10 OVERDOSAGE

Hyperphosphatemia

Administration of excessive doses of intravenous potassium phosphates as a single-dose ranging from approximately 50 to 270 mmol phosphorus and/or at rapid infusion rates (over 1 to 3 hours) has resulted in death, cardiac arrest, cardiac arrhythmia (including QT prolongation), hyperkalemia, hyperphosphatemia, seizures and tetany.

Hyperphosphatemia is particularly a risk in patients with renal failure. Hyperphosphatemia leads in turn to hypocalcemia, which may be severe and to ectopic calcification, particularly in patients with initial hypercalcemia. Tissue calcification may cause hypotension and organ damage and result in acute renal failure.

Hyperkalemia

Excessive administration of phosphates given as potassium salts may also cause hyperkalemia. Manifestations of hyperkalemia include:

- Disturbances in cardiac conduction and arrhythmias, including bradycardia, heart block, asystole, ventricular tachycardia, ventricular fibrillation.
- Hypotension.
- Muscle weakness including paresthesia, muscular and respiratory paralysis.

Management

In the event of overdosage, discontinue infusions containing potassium phosphates immediately and institute general supportive measures, including ECG monitoring, laboratory monitoring and correction of serum electrolyte concentrations, especially potassium, phosphorus, calcium and magnesium.

11 DESCRIPTION

Potassium Phosphates in 0.9% Sodium Chloride Injection, for intravenous use, is a phosphorus replacement product containing phosphorus 0.06 mmol/mL and potassium 0.088 mEq/mL. It is a sterile, non-pyrogenic, ready-to-use diluted solution containing a mixture of monobasic potassium phosphate, USP and dibasic potassium phosphate, USP in 0.9% sodium chloride. No dilution is required before administration. It is supplied in 250 mL single-dose intravenous infusion bag.

Monobasic Potassium Phosphate is chemically designated KH2PO4, molecular weight 136.09, white, odorless crystals or granules freely soluble in water.

Dibasic Potassium Phosphate is chemically designated K2HPO4, molecular weight 174.18, colorless or white granular salt freely soluble in water.

Each mL contains 4.48 mg of monobasic potassium phosphate, USP and 4.72 mg of dibasic potassium phosphate, USP.

Each mL contains phosphorus, 0.06 mmol (equivalent to 1.86 mg phosphorus); potassium, 0.088 mEq (equivalent to 3.40 mg of potassium); sodium chloride, USP, 9 mg and water for injection, USP (q.s.).

Note: 1 mmol of phosphorus is equal to 1 mmol phosphate.

This product contains no more than 25 mcg/L of aluminum.

The pH is 5.8 to 7.2 and the osmolarity is 0.455 mOsmol/mL (calc).

12 CLINICAL PHARMACOLOGY

12.1 Mechanism of Action

Phosphorus in the form of organic and inorganic phosphate has a variety of biochemical functions in all organs and tissues, including critical roles in nucleic acid structure, energy storage and transfer, cell signaling, cell membrane composition and structure, acid-base balance, mineral homeostasis, and bone mineralization.

12.2 Pharmacodynamics

The exposure-response relationship and time course of pharmacodynamic response for the safety and effectiveness of potassium phosphates have not been fully characterized.

12.3 Pharmacokinetics

Distribution

Approximately 85% of serum phosphates is free and ultra-filterable and 15% is protein-bound.

Elimination

Intravenously infused phosphates not taken up by the tissues are excreted almost entirely in the urine. Serum phosphorus is believed to be filterable by the renal glomeruli and the major portion of filtered phosphorus (greater than 80%) is actively reabsorbed by the tubules.

16 HOW SUPPLIED/STORAGE AND HANDLING

Potassium Phosphates in 0.9% Sodium Chloride Injection is a clear, colorless solution filled in an intravenous infusion bag containing phosphorus 15 mmol/250 mL (0.06 mmol/mL) and potassium 22mEq/250mL (0.088 mEq/mL). It is supplied as:

One 250 mL Single-dose Infusion Bag in a Pouch: NDC 70121-1722-1

24 Pouches in a Shipper (Unit of sale): NDC 70121-1722-9

Store at 20°C to 25°C (68°F to 77°F); excursions permitted between 15°C to 30°C (59°F to 86°F) [see USP Controlled Room Temperature]. Keep covered in a pouch until time of use.

Each ready-to-use infusion bag contains no preservatives. Once the ready-to-use infusion bag has been removed from the pouch, the ready-to-use infusion bag should be used within 24 hours, with any unused portion discarded.

17 PATIENT COUNSELING INFORMATION

Inform patients, caregivers, or home healthcare providers of the following risks of Potassium Phosphates in Sodium Chloride Injection:

- Advise patients of the serious cardiac risks (e.g., death, cardiac arrest, cardiac arrhythmia, hyperkalemia, hyperphosphatemia, and seizures) associated with rapid administration of Potassium Phosphate in Sodium Chloride Injection [see Warnings and Precautions (5.1)].
- Advise patients that Potassium Phosphate in Sodium Chloride Injection may increase the risk of hyperkalemia when administered in excessive doses or by rapid intravenous infusion [see Warnings and Precautions (5.3)].
- Advise patients that hyperphosphatemia can occur, especially in patients with renal impairment, which can result in hypocalcemia [see Warnings and Precautions (5.4)].
- Advise patients that Potassium Phosphate in Sodium Chloride Injection has been reported to cause hypomagnesemia when administered to patients with hypercalcemia and diabetic ketoacidosis [see Warnings and Precautions (5.5)].

For additional information go to www.amneal.com or call 1-877-835-5472.

Manufactured by:

Amneal Pharmaceuticals Pvt. Ltd.

Mehsana 382165, INDIA

Or

Amneal Pharmaceuticals Pvt. Ltd.

Ahmedabad 382110, INDIA

Distributed by:

Amneal Pharmaceuticals LLC

Bridgewater, NJ 08807

Rev. 09-2025-02

PRINCIPAL DISPLAY PANEL

NDC 70121-1722-1 (Palli)

Potassium Phosphates in 0.9% Sodium Chloride Injection

Phosphorus 15 mmol/250 mL (0.06 mmol/ mL)

Potassium 22 mEq/250 mL (0.088 mEq/mL)

Intravenous Bag Label

Rx only

Amneal Pharmaceuticals LLC

NDC 70121-1722-1 (Palli)

Potassium Phosphates in 0.9% Sodium Chloride Injection

Phosphorus 15 mmol/250 mL (0.06 mmol/ mL)

Potassium 22 mEq/250 mL (0.088 mEq/mL)

Pouch Label

Rx only

Amneal Pharmaceuticals LLC

NDC 70121-1722-9 (Palli)

Potassium Phosphates in 0.9% Sodium Chloride Injection

Phosphorus 15 mmol/250 mL (0.06 mmol/ mL)

Potassium 22 mEq/250 mL (0.088 mEq/mL)

Carton Label

Rx only

Amneal Pharmaceuticals LLC

NDC 70121-1722-1 (Pipan)

Potassium Phosphates in 0.9% Sodium Chloride Injection

Phosphorus 15 mmol/250 mL (0.06 mmol/ mL)

Potassium 22 mEq/250 mL (0.088 mEq/mL)

Intravenous Bag Label

Rx only

Amneal Pharmaceuticals LLC

NDC 70121-1722-1 (Pipan)

Potassium Phosphates in 0.9% Sodium Chloride Injection

Phosphorus 15 mmol/250 mL (0.06 mmol/ mL)

Potassium 22 mEq/250 mL (0.088 mEq/mL)

Pouch Label

Rx only

Amneal Pharmaceuticals LLC

NDC 70121-1722-9 (Pipan)

Potassium Phosphates in 0.9% Sodium Chloride Injection

Phosphorus 15 mmol/250 mL (0.06 mmol/ mL)

Potassium 22 mEq/250 mL (0.088 mEq/mL)

Carton Label

Rx only

Amneal Pharmaceuticals LLC